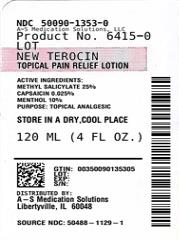 DRUG LABEL: NEW TEROCIN
NDC: 50090-1353 | Form: LOTION
Manufacturer: A-S Medication Solutions
Category: otc | Type: HUMAN OTC DRUG LABEL
Date: 20250109

ACTIVE INGREDIENTS: METHYL SALICYLATE 25 g/100 mL; CAPSAICIN 0.025 g/100 mL; MENTHOL 10 g/100 mL
INACTIVE INGREDIENTS: ALOE BARBADENSIS LEAF JUICE; WATER; PROPYLENE GLYCOL; ALKYL (C12-15) BENZOATE; CETOSTEARYL ALCOHOL; CETYL ALCOHOL; DIAZOLIDINYL UREA; STEARIC ACID; GLYCERYL MONOSTEARATE; PEG-100 MONOSTEARATE; POLYSORBATE 20; POLYSORBATE 60; DIMETHYL SULFONE; LAVANDULA ANGUSTIFOLIA (LAVENDER) OIL; BORAGE OIL; BOSWELLIA SERRATA GUM; XANTHAN GUM; TROLAMINE; METHYLPARABEN; PROPYLPARABEN; DMDM HYDANTOIN; STEARYL ALCOHOL

NEW TEROCIN

Active ingredients:

Methyl Salicylate 25%
Capsaicin 0.025%
Menthol 10%

Purpose

Topical Analgesic

Uses:

Temporarily relieves mild aches and pains of muscles or joints.

Warnings

Only for external use.

Do Not Use:

on open wounds, cuts, damaged or infected skin as well as in the eyes, mouth, genitals, or any other mucous membranes.

Consult your physician:

if pain is persistent or worsens or if using any other topical pain products.

Keep out of reach of children.

Consult physician for children under 12.

Directions:

Wash and dry affected area. Shake bottle well before each use and gently rub over area of pain. Use is not recommended more than four times a day. Wash hands immediately afterwards to avoid contact with eyes.

Inactive Ingredients:

Aloe Barbadensis Leaf (Aloe Vera Gel) Juice, Aqua (Deionized Water), Borago Officinalis (Borage) Seed Oil, Boswellia Serrata Extract, C12-15 Alkyl Benzoate, Cetearyl Alcohol, Cetyl Alcohol, Diazolidinyl Urea, Dimethyl Sulfone (DMSO), DMDM Hydantoin, Glyceryl Stearate, Lavandula Angustifolia (Lavender) Oil, Methyl Paraben, PEG-100 Stearate, Polysorbate-20, Polysorbate-60, Propyl Paraben, Propylene Glycol, Stearic Acid, Stearyl Alcohol, Triethanolamine, Xanthan Gum.

HOW SUPPLIED

Product: 50090-1353

NDC: 50090-1353-0 120 mL in a BOTTLE